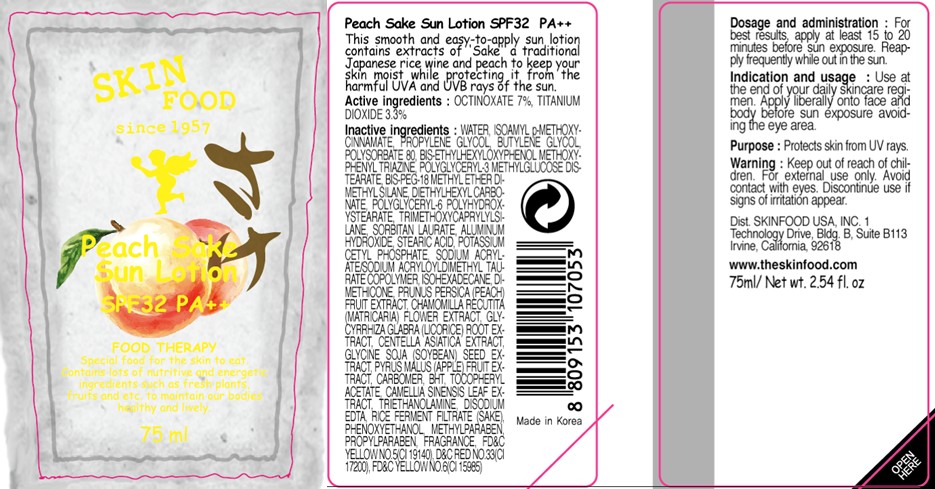 DRUG LABEL: PEACH SAKE SUN
NDC: 76214-012 | Form: LOTION
Manufacturer: SKINFOOD CO., LTD.
Category: otc | Type: HUMAN OTC DRUG LABEL
Date: 20110907

ACTIVE INGREDIENTS: OCTINOXATE 5.25 mL/75 mL; TITANIUM DIOXIDE 2.47 mL/75 mL
INACTIVE INGREDIENTS: WATER; PROPYLENE GLYCOL; BUTYLENE GLYCOL; POLYSORBATE 80; DIETHYLHEXYL CARBONATE; TRIMETHOXYCAPRYLYLSILANE; SORBITAN MONOLAURATE; ALUMINUM HYDROXIDE; STEARIC ACID; POTASSIUM CETYL PHOSPHATE; ISOHEXADECANE; DIMETHICONE; PHENOXYETHANOL; METHYLPARABEN; PEACH; PROPYLPARABEN; CHAMOMILE; GLYCYRRHIZA GLABRA; CENTELLA ASIATICA; SOYBEAN; APPLE; BUTYLATED HYDROXYTOLUENE; TROLAMINE; EDETATE DISODIUM

Drug Facts

Active Ingredients: OCTINOXATE 7%, TITANIUM DIOXIDE 3.3%

Inactive ingredients:
WATER, ISOAMYL p-METHOXYCINNAMATE, PROPYLENE GLYCOL, BUTYLENE GLYCOL, POLYSORBATE 80, BIS-ETHYLHEXYLOXYPHENOL METHOXYPHENYL TRIAZINE, POLYGLYCERYL-3 METHYLGLUCOSE DISTEARATE, BIS-PEG-18 METHYL ETHER DIMETHYL SILANE, DIETHYLHEXYL CARBONATE, POLYGLYCERYL-6 POLYHYDROXYSTEARATE, RIMETHOXYCAPRYLYLSILANE, SORBITAN LAURATE, ALUMINUM HYDROXIDE, STEARIC ACID, POTASSIUM CETYL PHOSPHATE, SODIUM ACRYLATE/SODIUM ACRYLOYLDIMETHYL TAURATE COPOLYMER, ISOHEXADECANE, DIMETHICONE, PRUNUS PERSICA (PEACH) FRUIT EXTRACT, CHAMOMILLA RECUTITA (MATRICARIA) FLOWER EXTRACT, GLYCYRRHIZA GLABRA (LICORICE) ROOT EXTRACT, CENTELLA ASIATICA EXTRACT, GLYCINE SOJA (SOYBEAN) SEED EXTRACT, PYRUS MALUS (APPLE) FRUIT EXTRACT, CARBOMER, BHT, TOCOPHERYL ACETATE, CAMELLIA SINENSIS LEAF EXTRACT, TRIETHANOLAMINE, DISODIUM EDTA, RICE FERMENT FILTRATE (SAKE), PHENOXYETHANOL, METHYLPARABEN, PROPYLPARABEN, FRAGRANCE

Purpose: Protects skin from UV rays.

Warnings:
For external use only. Avoid contact with eyes.
Discontinue use if signs of irritation appear.

Keep out of reach of children:
Keep out of reach of children.

Indication and usage:
Use at the end of your daily skincare regimen. Apply liberally onto face and body before sun exposure avoiding the eye area.

Dosage and administration:
For best results, apply at least 15 to 20 minutes before sun exposure.
Reapply frequently while out in the sun.